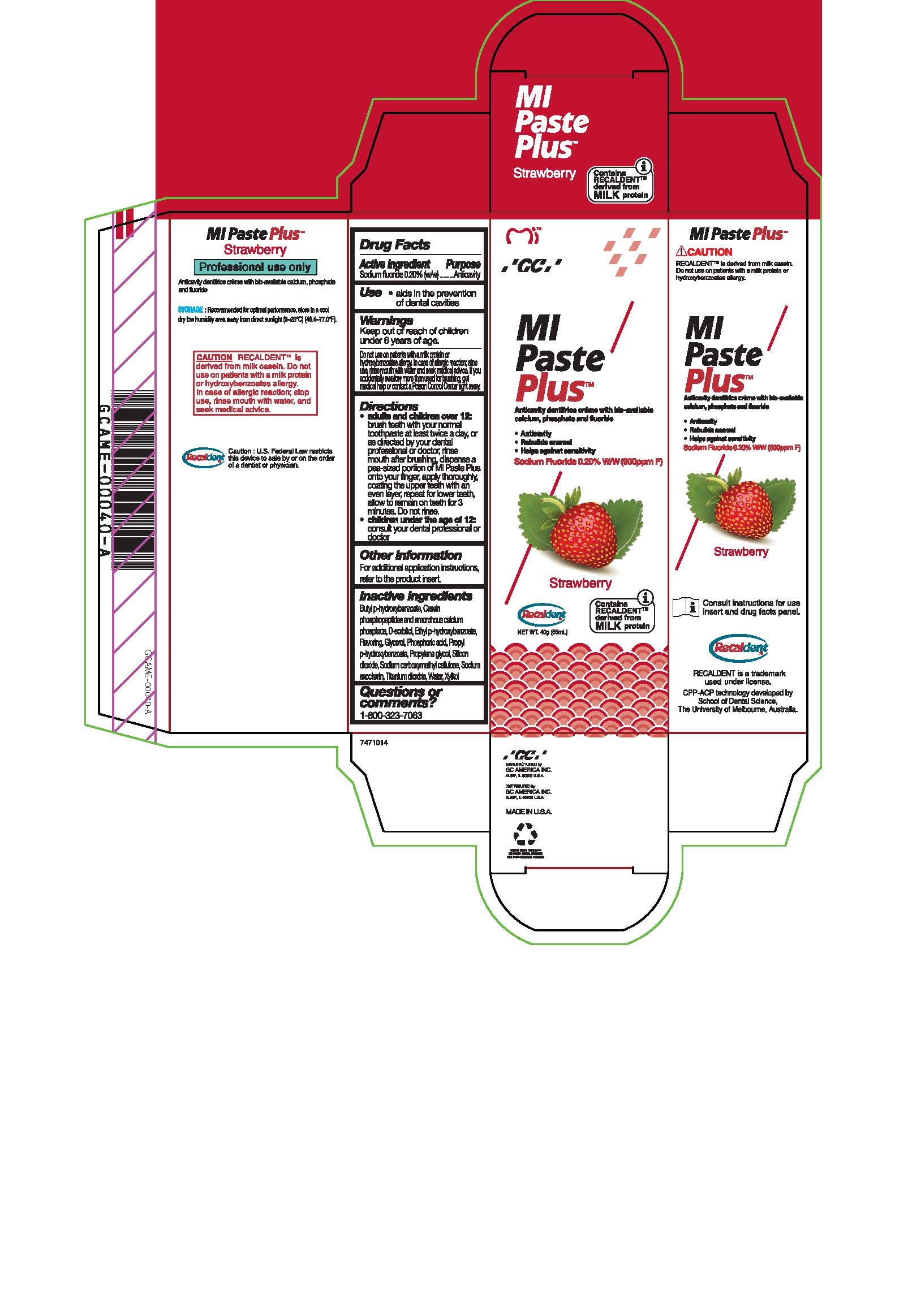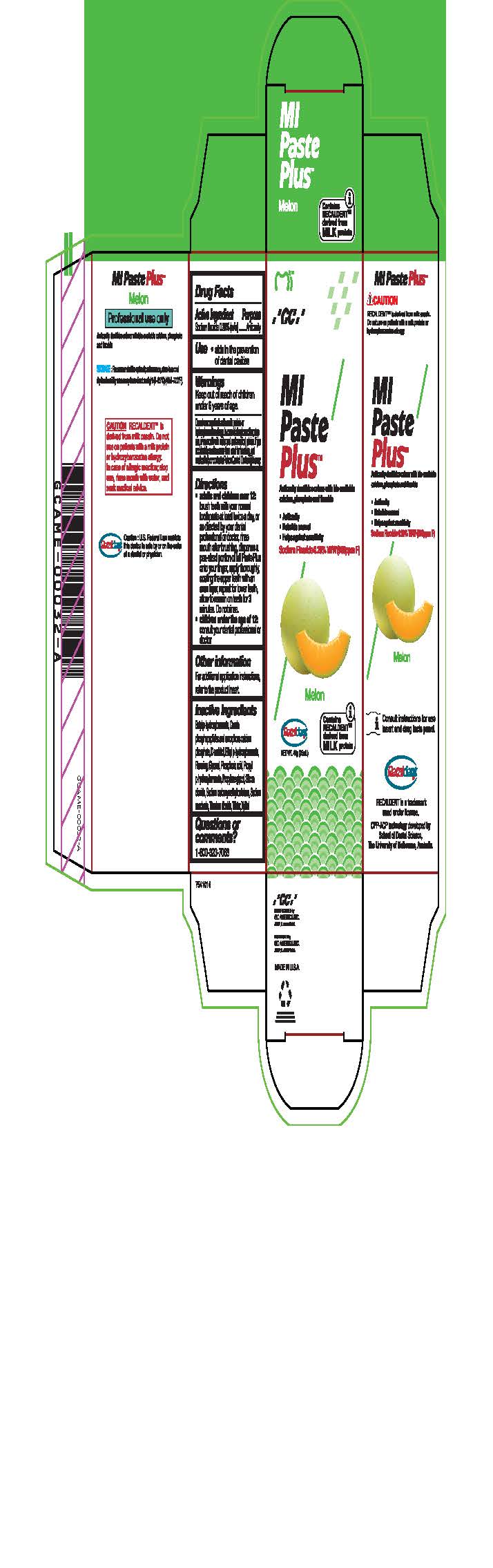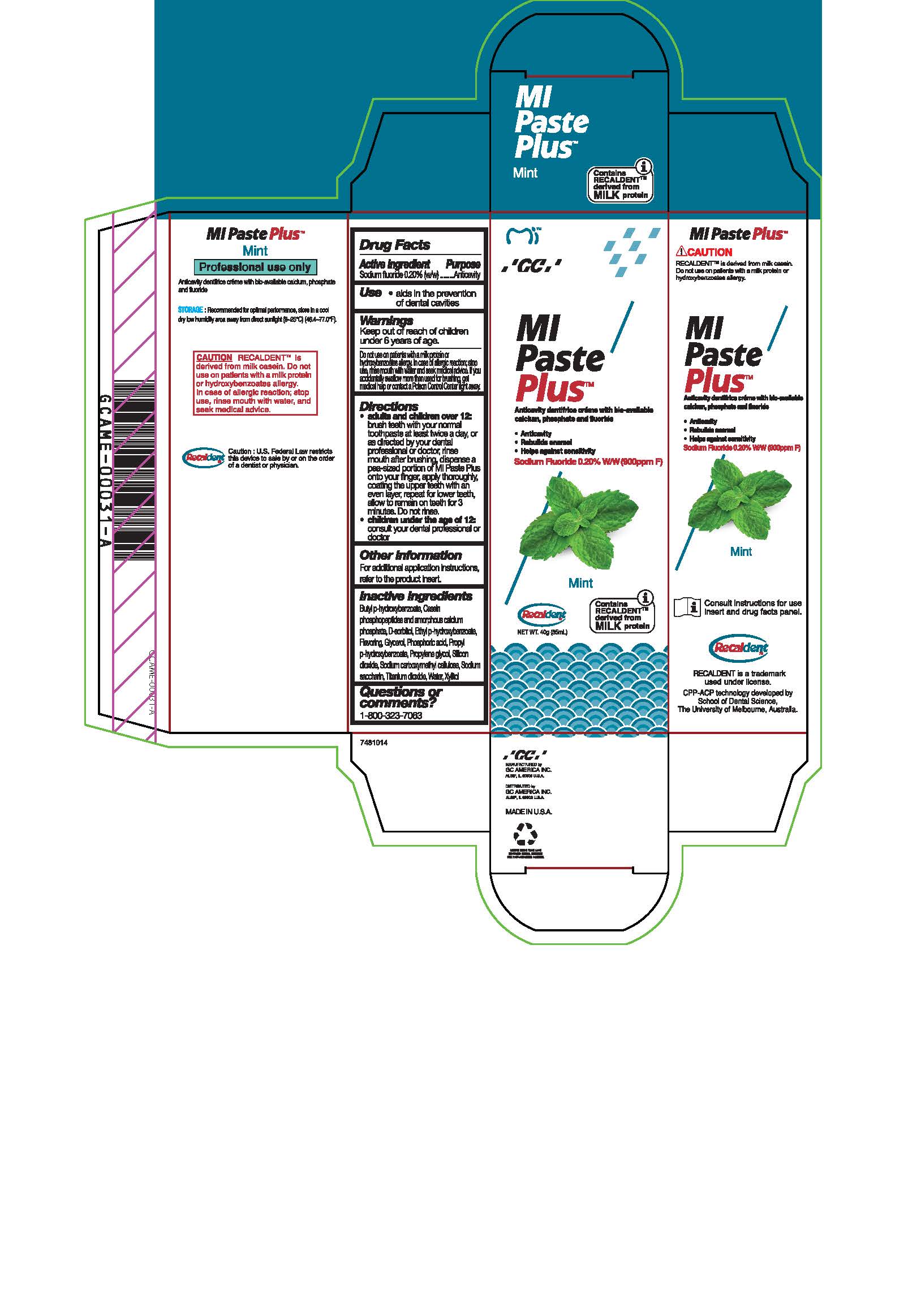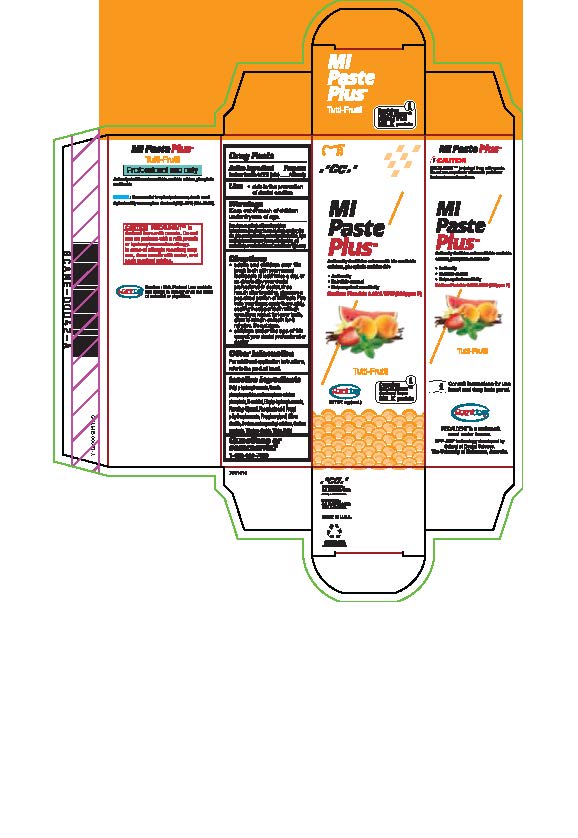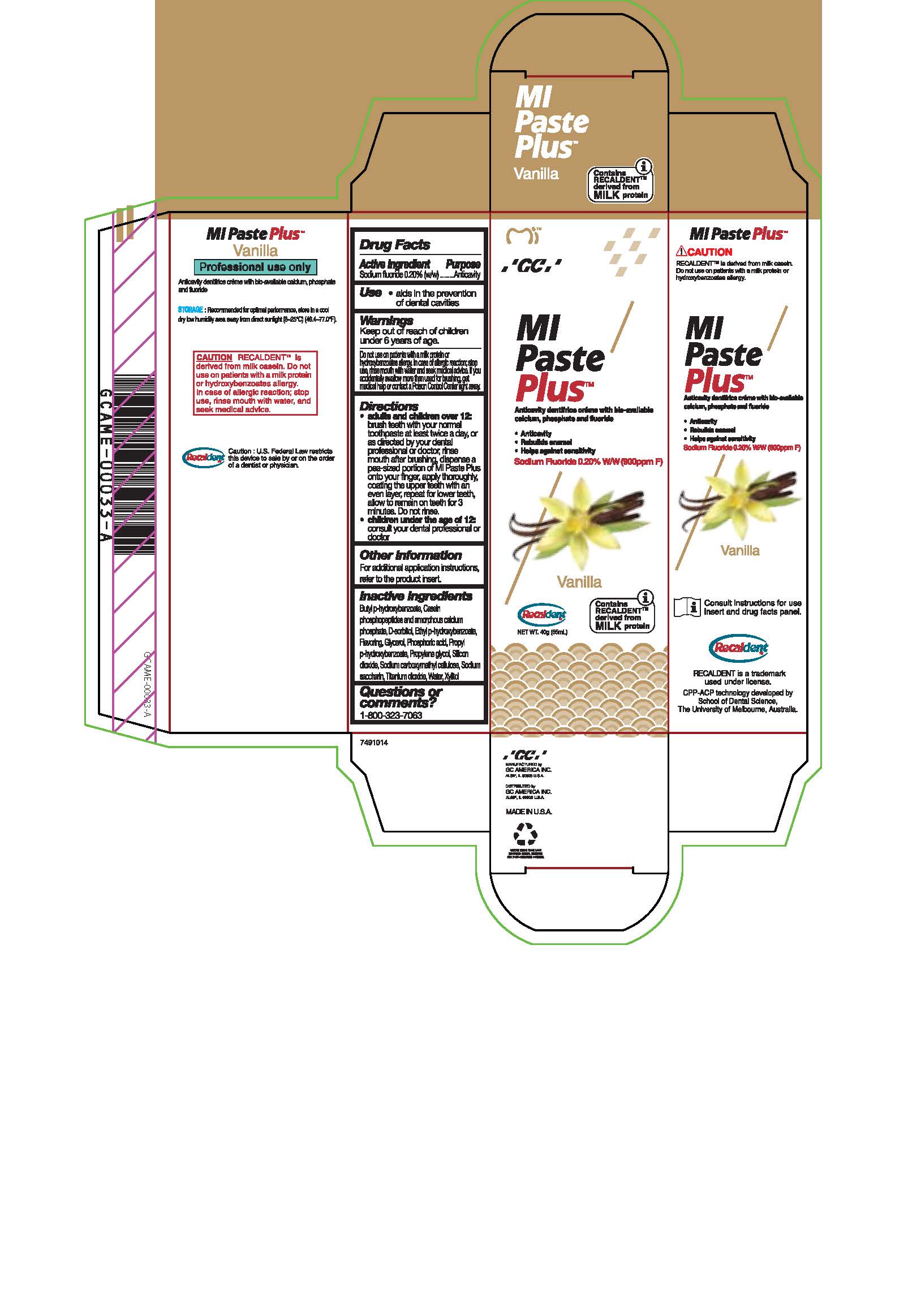 DRUG LABEL: MIPaste Plus Strawberry
NDC: 61596-986 | Form: PASTE, DENTIFRICE
Manufacturer: GC America Inc.
Category: otc | Type: HUMAN OTC DRUG LABEL
Date: 20251219

ACTIVE INGREDIENTS: SODIUM FLUORIDE 0.2 g/100 g
INACTIVE INGREDIENTS: CARBOXYMETHYLCELLULOSE SODIUM, UNSPECIFIED FORM; SORBITOL; WATER; GLYCERIN; PROPYLPARABEN; PHOSPHORIC ACID; SACCHARIN SODIUM; TITANIUM DIOXIDE; ETHYLPARABEN; CALCIUM PHOSPHATE; PROPYLENE GLYCOL; XYLITOL; BUTYLPARABEN; SILICON DIOXIDE

MIPaste Plus Strawberry

Active Ingredient

Sodium Fluoride 0.2% (w/w)............Anticavity

Use

Aids in the prevention of dental cavities

Warnings

Keep out of reach of children under 6 years of age.

Warnings

Do not use on patients with a milk protein or hydroxybenzoates allergy. In case of allergic reaction, stop use, rinse mouth with water and seek medical advice. If you accidentally swallow more than used for brushing, get medical help or contact a Poison Control Center right away.

Directions

* Adults and children over 12: brush teeth with your normal toothpaste at least twice a day, or as directed by your dental profession or doctor, rinse mouth after brushing, dispense a pea-sized portion of MI Paste Plus onto your finger, apply thoroughly, coating the upper teeth with an even layer, repeat for lower teeth, allow to remain on teeth for 3 mintues. Do not rinse.

* Children under the age of 12: consult your dental professional or doctor.

Other information

For additional application instructions, refer to the product insert.

Inactive ingredients

Butyl p-hydroxybenzoate, Casein phosphopeptides and amorphous calcium phosphate, D-sorbitol, Ethyl p-hydroxybenzoate, Flavoring, Glycerol, Phosphoric acid, Propyl p-hydroxybenzoate, Propylene glycol, Silicon dioxide, sodium carboxymethyl cellulose, Sodium saccharin, Titanium dioxide, Water, Xylitol

Questions or comments?

1-800-323-7063

Recommended Indications

To be used for cleaning and polishing procedures as part of a professionally administered prophylaxis treatment. Secondarily, MI Paste Plus can be used for the management of tooth sensitivity, post-scaling, root planing and bleaching.